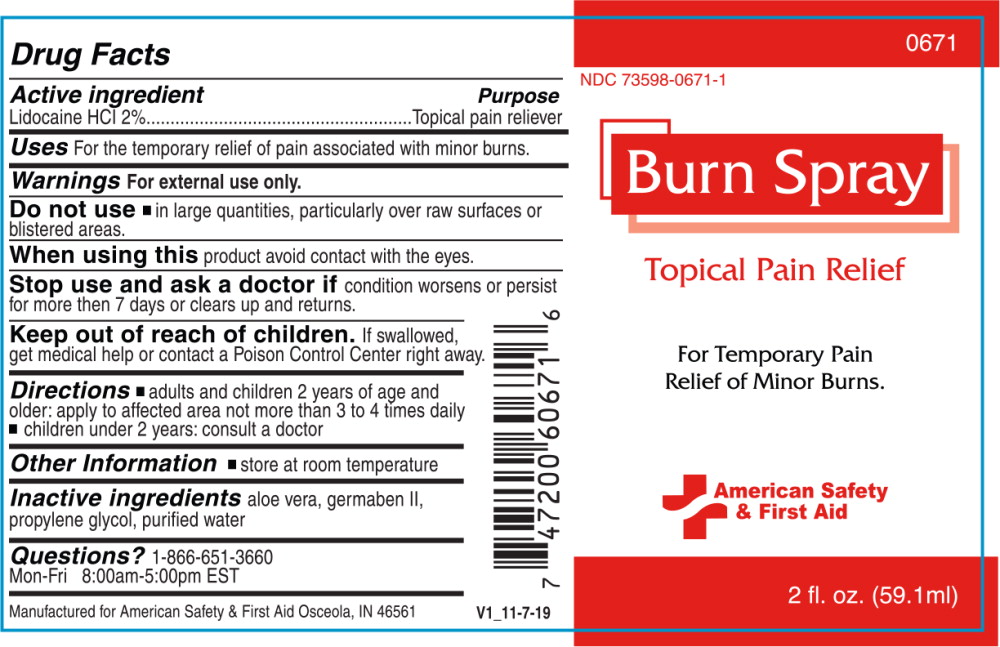 DRUG LABEL: Burn
NDC: 73598-0671 | Form: SPRAY
Manufacturer: JHK Inc
Category: otc | Type: HUMAN OTC DRUG LABEL
Date: 20240425

ACTIVE INGREDIENTS: LIDOCAINE HYDROCHLORIDE 20 mg/1 mL
INACTIVE INGREDIENTS: aloe vera leaf; propylene glycol; diazolidinyl urea; water

Drug Facts

Active ingredient

Lidocaine HCl 2%

Purpose

Topical pain reliever

Uses

For the temporary relief of pain associated with minor burns.

Warnings

For external use only.

Do not use

- in large quantities, particularly over raw surfaces or blistered areas.

When using this product avoid contact with the eyes.

Stop use and ask a doctor if condition worsens or persist for more then 7 days or clears up and returns.

Keep out of reach of children. If swallowed, get medical help or contact a Poison Control Center right away.

Directions

- adults and children 2 years of age and older: apply to affected area not more than 3 to 4 times daily
- children under 2 years: consult a doctor

Other information

- store at room temperature

Inactive ingredients

Aloe vera, germaben II, propylene glycol, purified water

Questions?

1-866-651-3660

Mon-Fri 8:00am-5:00pm EST

Manufactured for American Safety & First Aid Osceola, IN 46561

V1_11-7-19

Principal Display Panel – Bottle Label

0671

NDC 73598-0671-1

Burn Spray

Topical Pain Relief

For Temporary Pain
Relief of Minor Burns.

American Safety
& First Aid

2 fl. Oz. (59.1 ml)